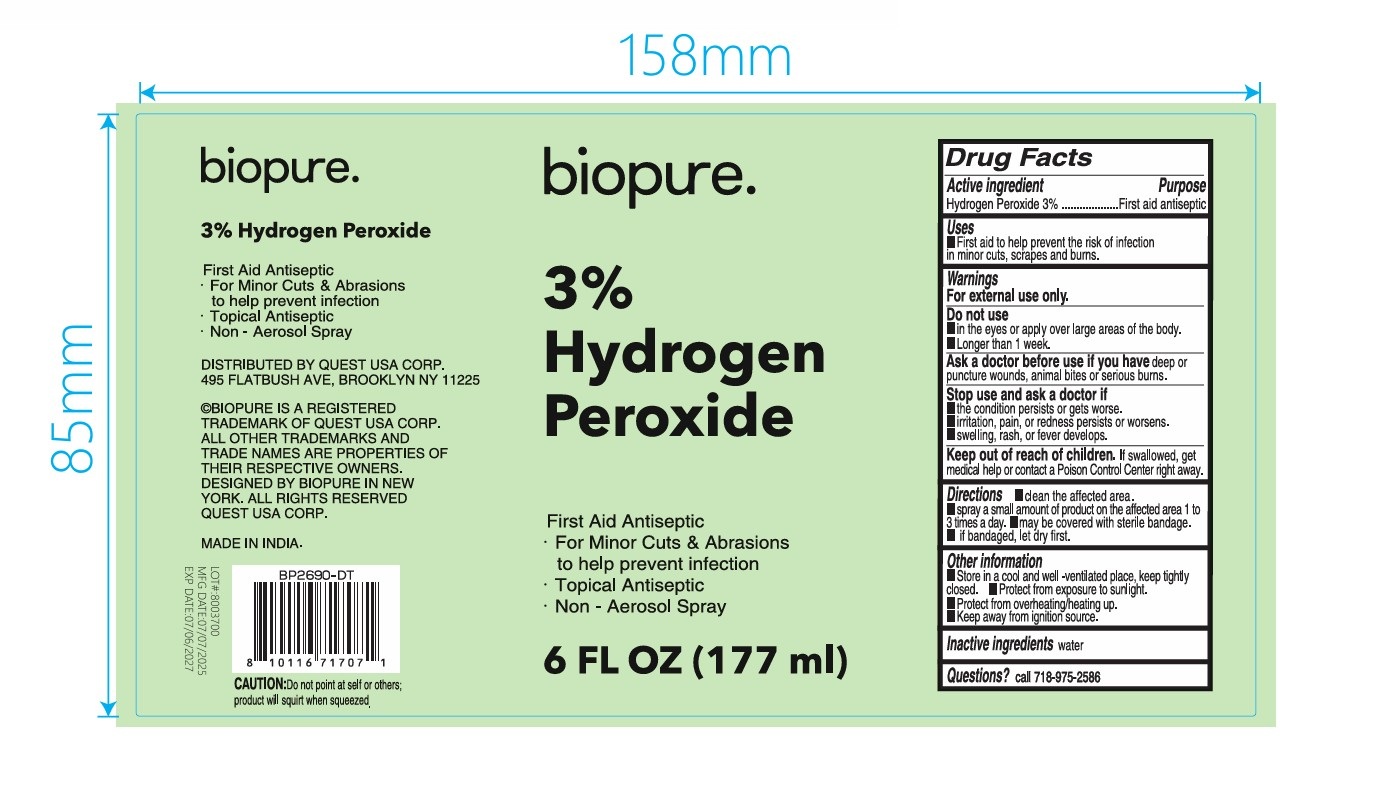 DRUG LABEL: Biopure 3 Hydrogen Peroxide
NDC: 78691-021 | Form: LIQUID
Manufacturer: Quest USA Corp
Category: otc | Type: HUMAN OTC DRUG LABEL
Date: 20250602

ACTIVE INGREDIENTS: HYDROGEN PEROXIDE 30 mg/1 mL
INACTIVE INGREDIENTS: WATER

Biopure 3% Hydrogen Peroxide

Active ingredients

Hydrogen Peroxide 3%

Purpose

First aid antiseptic

Uses

- First aid to help prevent the risk of infection in minor cuts, scrapes and burns.

Warnings

For external use only.

Do not use

- in the eyes or apply over large areas of the body.
- Longer than 1 week.

Ask a doctor before use if you have

deep or punture wounds, animal bites or serious burns.

Stop use and ask a doctor if

- the condition persists or gets worse.
- irritation, pain, or rendess persists or worsens.
- swelling, rash, or fever develops.

Keep out of reach of children.

If swallowed, get medical help or contact a Poison Control Center right away.

Directions

- clean the affected area.
- spray a small amount of product on the affected area 1 to 3 times a day.
- may be covered with sterile bandage.
- if bandaged, let dry first.

Other information

- Store in a cool and well-ventillated place, keep tightly closed.
- Protect from exposure to sunlight.
- Protect from overheating/heating up.
- Keep away from ignition source.

Inactive ingredients

water

Questions?

call 718-975-2586